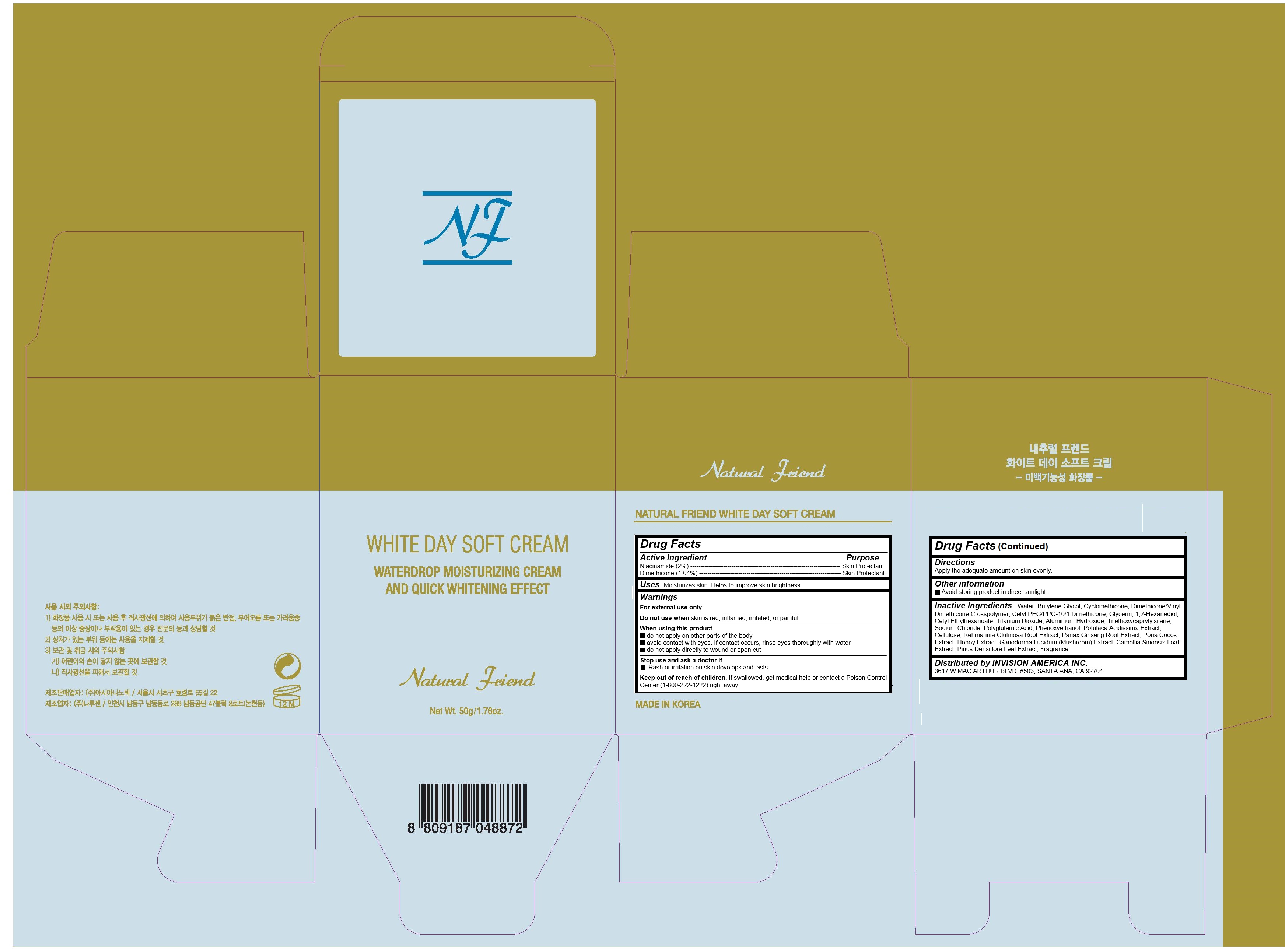 DRUG LABEL: Natural Friend White Day Soft Cream
NDC: 71623-100 | Form: CREAM
Manufacturer: Asia Nanotech Co., Ltd.
Category: otc | Type: HUMAN OTC DRUG LABEL
Date: 20181214

ACTIVE INGREDIENTS: NIACINAMIDE 1 g/50 g; DIMETHICONE 0.52 g/50 g
INACTIVE INGREDIENTS: WATER; DIMETHICONE/VINYL DIMETHICONE CROSSPOLYMER (SOFT PARTICLE); SODIUM CHLORIDE; REHMANNIA GLUTINOSA ROOT; ASIAN GINSENG; FU LING; REISHI; BUTYLENE GLYCOL; CYCLOMETHICONE; GLYCERIN; GREEN TEA LEAF; 1,2-HEXANEDIOL; CETYL ETHYLHEXANOATE; TITANIUM DIOXIDE; ALUMINUM HYDROXIDE; TRIETHOXYCAPRYLYLSILANE; PHENOXYETHANOL; POWDERED CELLULOSE; HONEY; PINUS DENSIFLORA LEAF

Natural Friend White Day Soft Cream

Active Ingredients

Niacinamide (2%)

Dimethicone (1.04%)

Purpose

Skin Protectant

Uses

Moisturizes skin. Helps to improve skin brightness.

Warnings

For external use only

Do not use when skin is red, inflamed, irritated, or painful

When using this product

- do not apply on other parts of the body

- avoid contact with eyes. If contact occurs, rinse eyes thoroughly with water

- do not apply directly to wound or open cut

Stop use and ask a doctor if

- Rash or irritation on skin develops and lasts

Keep out of reach of children

If swallowed, get medical help or contact a Poison Control Center (1-800-222-1222) right away.

Directions

Apply the adequate amount on skin evenly.

Inactive Ingredients

Water, Butylene Glycol, Cyclomethicone, Dimethicone/Vinyl Dimethicone Crosspolymer, Cetyl PEG/PPG-10/1 Dimethicone, Glycerin, 1,2-Hexanediol, Cetyl Ethylhexanoate, Titanium Dioxide, Aluminium Hydroxide, Triethoxycaprylylsilane, Sodium Chloride, Polyglutamic Acid, Phenoxyethanol, Potulaca Acidissima Extract, Cellulose, Rehmannia Glutinosa Root Extract, Panax Ginseng Root Extract, Poria Cocos Extract, Honey Extract, Ganoderma Lucidum (Mushroom) Extract, Camellia Sinensis Leaf Extract, Pinus Densiflora Leaf Extract, Fragrance